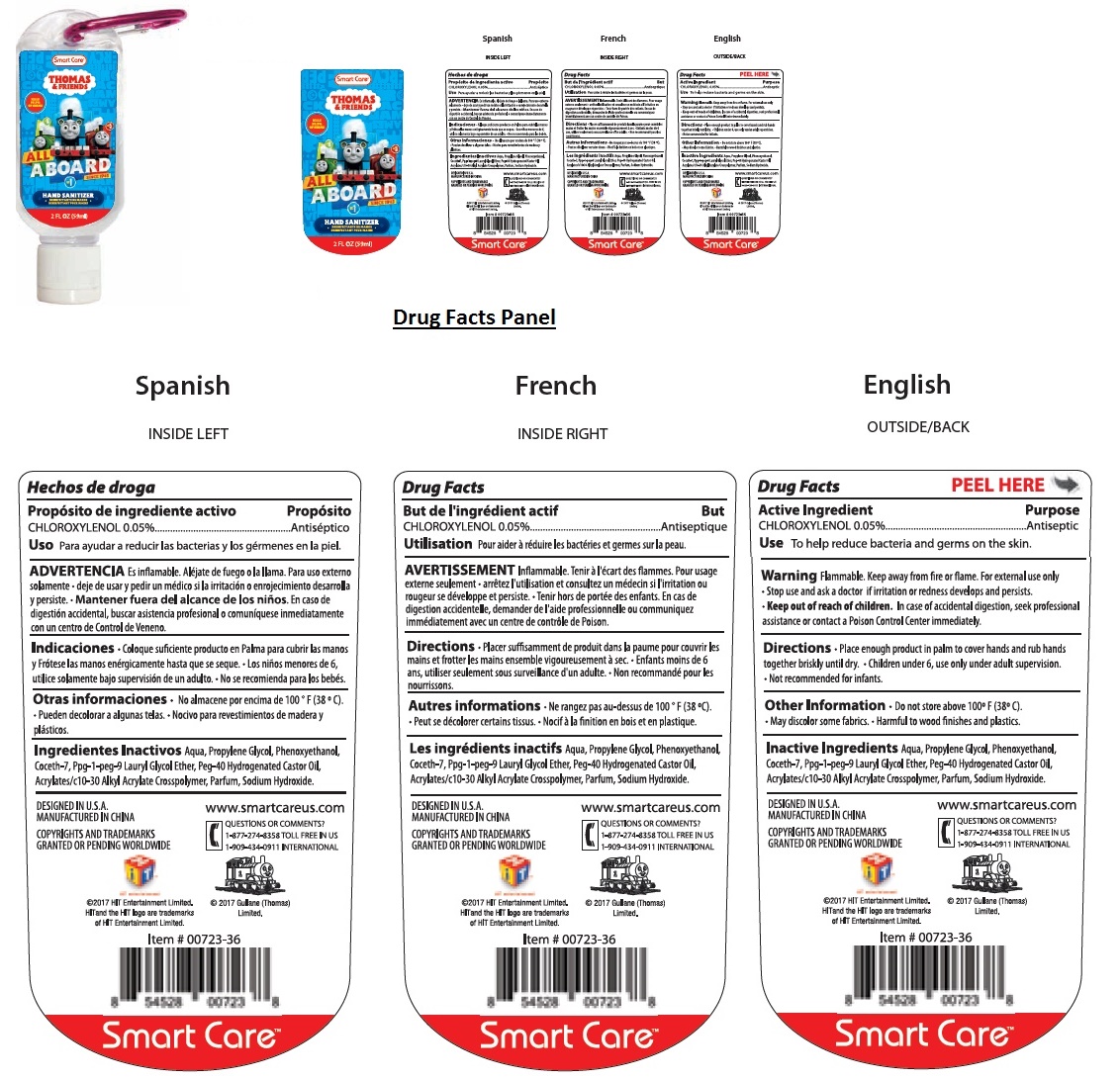 DRUG LABEL: THOMAS AND FRIENDS HAND SANITIZER
NDC: 70108-009 | Form: LIQUID
Manufacturer: Ashtel Studios, Inc
Category: otc | Type: HUMAN OTC DRUG LABEL
Date: 20191231

ACTIVE INGREDIENTS: CHLOROXYLENOL 0.05 g/100 mL
INACTIVE INGREDIENTS: WATER; PROPYLENE GLYCOL; PHENOXYETHANOL; COCETH-7; PPG-1-PEG-9 LAURYL GLYCOL ETHER; POLYOXYL 40 HYDROGENATED CASTOR OIL; CARBOMER INTERPOLYMER TYPE A (ALLYL SUCROSE CROSSLINKED); SODIUM HYDROXIDE

THOMAS AND FRIENDS HAND SANITIZER

Active Ingredient

CHLOROXYLENOL 0.05%

Purpose

Antiseptic

Use

To help reduce bacteria and germs on the skin.

Warning

Flammable. Keep away from fire or flame. For external use only

• Stop use and ask a doctor if irritation or redness develops and persists.

• Keep out of reach of children. In case of accidental digestion, seek professional assistance or contact a Poison Control Center immediately.

Directions

• Place enough product in palm to cover hands and rub hands together briskly until dry. • Children under 6, use only under adult supervision. • Not recommended for infants.

Inactive Ingredients

Aqua, Propylene Glycol, Phenoxyethanol, Coceth-7, Ppg-1-peg-9 Lauryl Glycol Ether, Peg-40 Hydrogenated Castor Oil, Acrylates/c10-30 Alkyl Acrylate Crosspolymer, Parfum, Sodium Hydroxide.

Other Information

• Do not store above 100° F (38° C). • May discolor some fabrics. • Harmful to wood finishes and plastics.

KILLS 99.9% OF GERMS

HAND SANITIZER
DESINFECTANTE DE MANOS
DESINFECTANT POUR MAINS

DESIGNED IN U.S.A.
MANUFACTURED IN CHINA
www.smartcareus.com
QUESTIONS OR COMMENTS?
1-877-274-8358 TOLL FREE IN US
1-909-434-0911 INTERNATIONAL